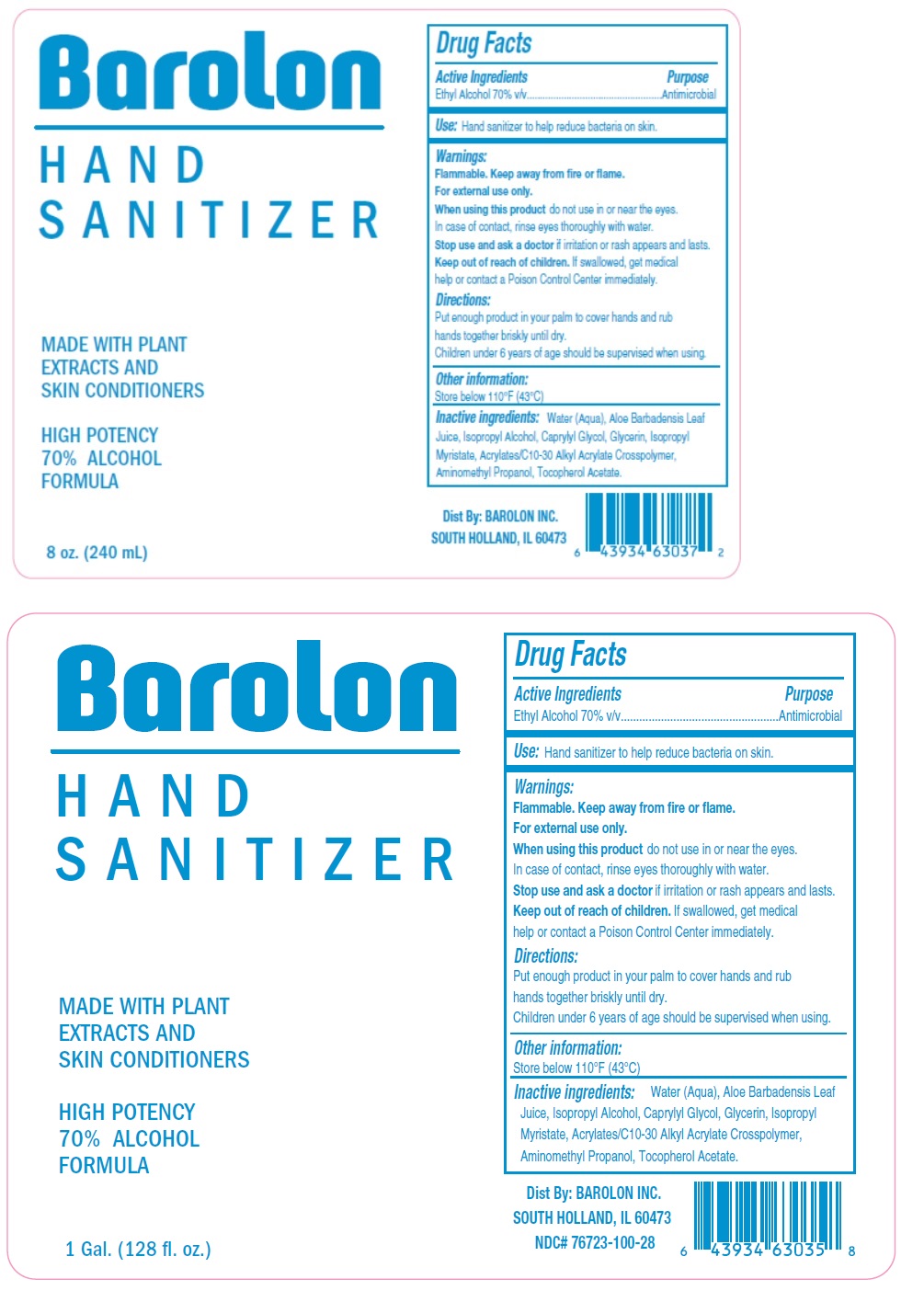 DRUG LABEL: Barolon HAND SANITIZER
NDC: 76723-100 | Form: GEL
Manufacturer: Barolon Labs
Category: otc | Type: HUMAN OTC DRUG LABEL
Date: 20200530

ACTIVE INGREDIENTS: ALCOHOL 70 mL/100 mL
INACTIVE INGREDIENTS: WATER; ALOE VERA LEAF; ISOPROPYL ALCOHOL; CAPRYLYL GLYCOL; GLYCERIN; ISOPROPYL MYRISTATE; CARBOMER INTERPOLYMER TYPE A (ALLYL SUCROSE CROSSLINKED); AMINOMETHYLPROPANOL; .ALPHA.-TOCOPHEROL ACETATE

Barolon HAND SANITIZER

Active Ingredients

Ethyl Alcohol 70% v/v

Purpose

Antimicrobial

Use:

Hand sanitizer to help reduce bacteria on skin.

Warnings:

Flammable. Keep away from fire or flame.
For external use only.
When using this product do not use in or near the eyes. In case of contact, rinse eyes thoroughly with water.
Stop use and ask a doctor if irritation or rash appears and lasts.

Keep out of reach of children. If swallowed, get medical help or contact a Poison Control Center immediately.

Directions:

Put enough product in your palm to cover hands and rub hands together briskly until dry.
Children under 6 years of age should be supervised when using.

Other information:

Store below 110°F (43°C)

Inactive ingredients:

Water (Aqua), Aloe Barbadensis Leaf Juice, Isopropyl Alcohol, Caprylyl Glycol, Glycerin, Isopropyl Myristate, Acrylates/C10-30 Alkyl Acrylate Crosspolymer, Aminomethyl Propanol, Tocopherol Acetate.

MADE WITH PLANT EXTRACTS AND SKIN CONDITIONERS

HIGH POTENCY 70% ALCOHOL FORMULA

Dist By: BAROLON INC. SOUTH HOLLAND, IL 60473